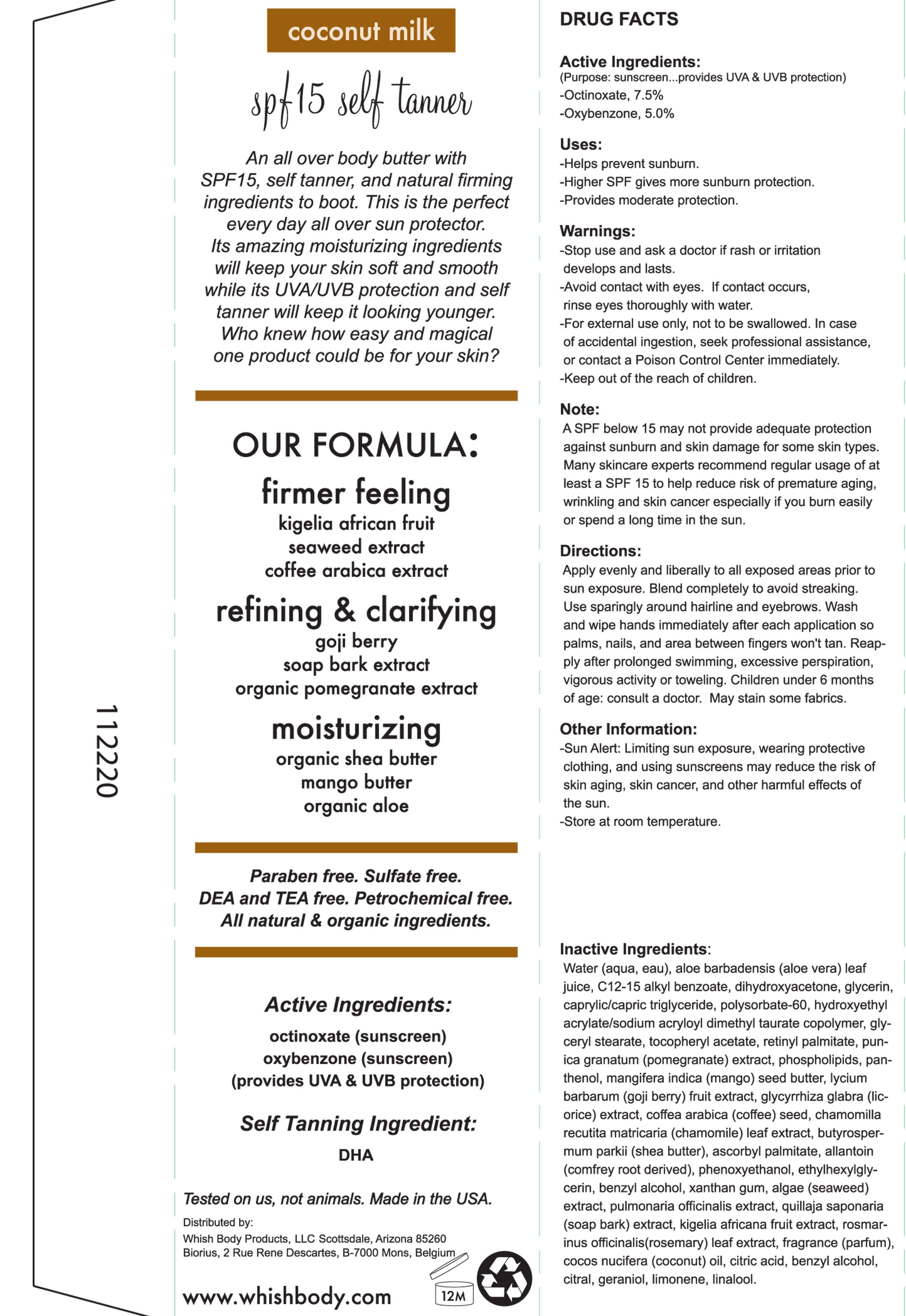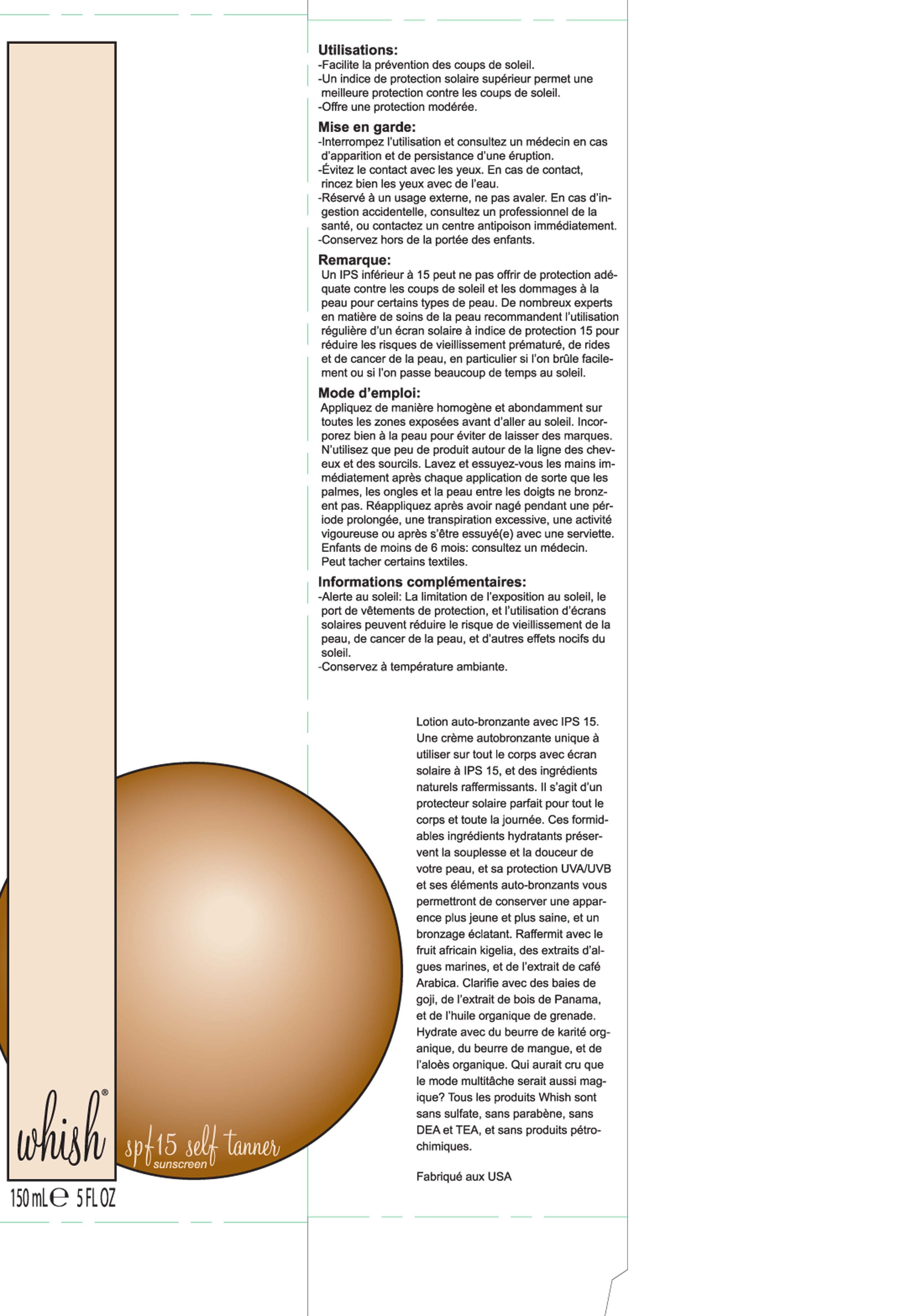 DRUG LABEL: SPF 15
NDC: 76224-101 | Form: LOTION
Manufacturer: Whish Body Holdings Inc
Category: otc | Type: HUMAN OTC DRUG LABEL
Date: 20110601

ACTIVE INGREDIENTS: OCTINOXATE 7.5 mL/100 mL; OXYBENZONE 5.0 mL/100 mL
INACTIVE INGREDIENTS: ALOE VERA LEAF; ALKYL (C12-15) BENZOATE; DIHYDROXYACETONE; GLYCERIN; MEDIUM-CHAIN TRIGLYCERIDES; POLYSORBATE 60; GLYCERYL MONOSTEARATE; VITAMIN A PALMITATE; POMEGRANATE; PANTHENOL; MANGIFERA INDICA SEED BUTTER; LYCIUM BARBARUM FRUIT; ARABICA COFFEE BEAN; SHEA BUTTER; COCONUT OIL; ALLANTOIN; PHENOXYETHANOL; ETHYLHEXYLGLYCERIN; BENZYL ALCOHOL; XANTHAN GUM; ROSEMARY; CITRIC ACID MONOHYDRATE; BENZYL ALCOHOL; CITRAL; GERANIOL; LIMONENE, (+)-; LINALOOL, (+)-

coconut milk SPF 15 Self Tanner

Active ingredients

Octinoxate 7.5 %

Oxybenzone 5.0%

PURPOSE

helps prevent sunburn

keep out of reach of children

INDICATIONS AND USAGE

for external use only

stop use and ask a doctor if rash or irritation develops and lasts.

avoid contact with eyes, if contact occurs, rinse eyes thoroughly with water.

INDICATIONS AND USAGE

apply evenly and liberally to all exposed areas prior to sun exposure.

INACTIVE INGREDIENT

Water (aqua), aloe barbadensis (aloe vera) leaf juice, C12-15 alkyl benzoate, dihydroxyacetone, glycerin, caprylic/ capric triglyceride, polysorbate-60, hydroxyethyl acrylates/ sodium acryloyl dimothyl taurate copolymer, glyceryl stearate , tocopheryl acetate, retinyl palmitate, punica granatum (pomegranate) extract, phospholipids, panthenol, mangifora indica (mango) seed butter,lyceum barbarum (goji berry) fruit extract,
glycynhiza glabra extract, coffea Arabica (coffee) seed, chamimilla recutita matricaria (chamomile) leaf extract, butyrospermum parkii (shea butter), ascorbyl palmitate, cocos nucifera(cocout) oil, allantoin ,phenoxyethanol, ethylhexylglycerin, benzyl alcohol, xanthan gum, algae (seaweed) extract, pulmonaria officinalis extract, quillaja saponaria (soap bark) extract, kigelia Africana fruit extract, rosmainus officinalis (rosemary) leaf extract, fragrance (parfum), citric acid,

PACKAGE LABEL

Whish

SPF 15 Self Tanner

150ml E FL. OZ